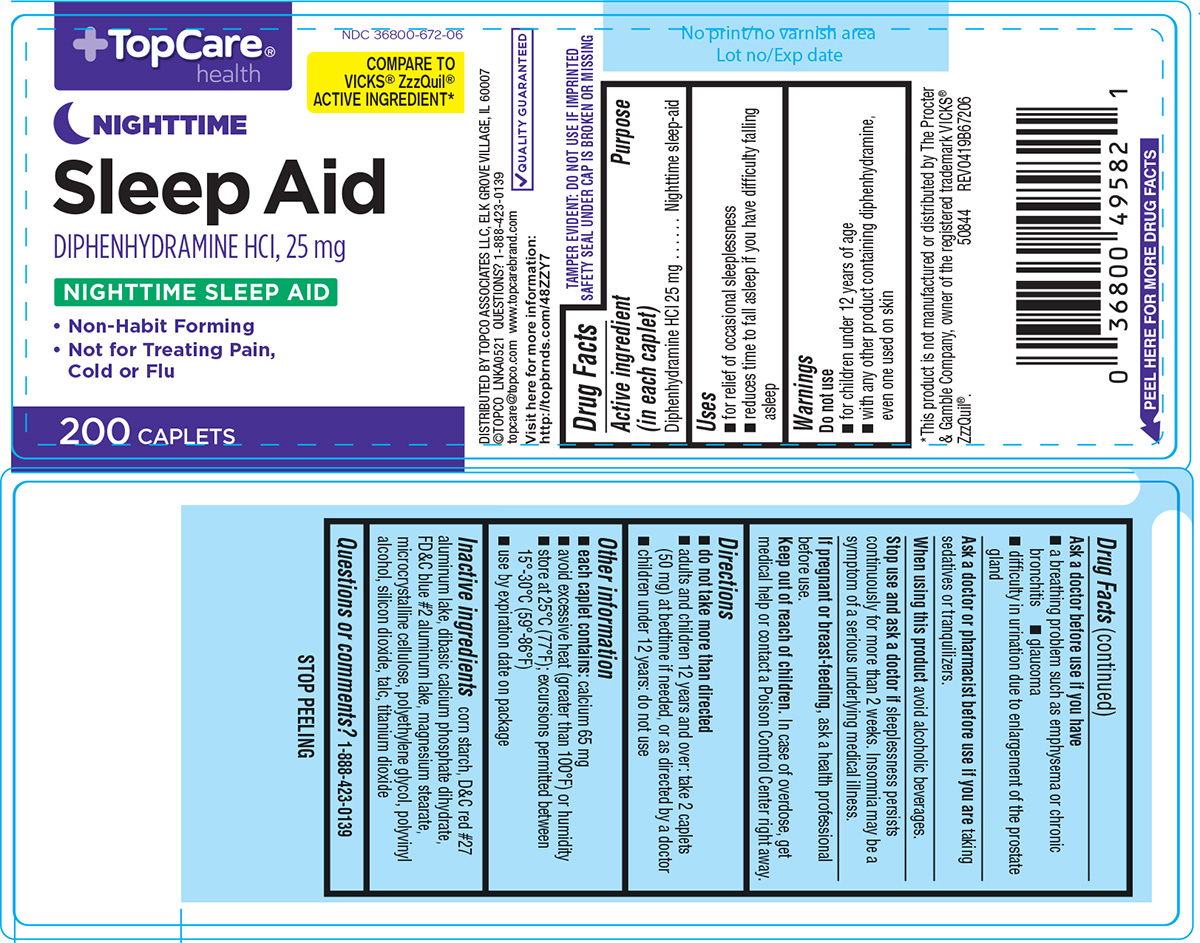 DRUG LABEL: Sleep Aid
NDC: 36800-672 | Form: TABLET, FILM COATED
Manufacturer: Topco Associates, LLC
Category: otc | Type: HUMAN OTC DRUG LABEL
Date: 20250612

ACTIVE INGREDIENTS: DIPHENHYDRAMINE HYDROCHLORIDE 25 mg/1 1
INACTIVE INGREDIENTS: STARCH, CORN; D&C RED NO. 27 ALUMINUM LAKE; DIBASIC CALCIUM PHOSPHATE DIHYDRATE; FD&C BLUE NO. 2 ALUMINUM LAKE; MAGNESIUM STEARATE; MICROCRYSTALLINE CELLULOSE; POLYETHYLENE GLYCOL, UNSPECIFIED; POLYVINYL ALCOHOL, UNSPECIFIED; SILICON DIOXIDE; TALC; TITANIUM DIOXIDE

TopCare 44-672

Active ingredient (in each caplet)

Diphenhydramine HCl 25 mg

Purpose

Nighttime sleep-aid

Uses

- for relief of occasional sleeplessness
- reduces time to fall asleep if you have difficulty falling asleep

Warnings

Do not use

- with any other product containing diphenhydramine, even one used on skin
- for children under 12 years of age

Ask a doctor before use if you have

- a breathing problem such as emphysema or chronic bronchitis
- glaucoma
- difficulty in urination due to enlargement of the prostate gland

Ask a doctor or pharmacist before use if you are

taking sedatives or tranquilizers.

When using this product

avoid alcoholic beverages.

Stop use and ask a doctor if

sleeplessness persists continuously for more than 2 weeks. Insomnia may be a symptom of a serious underlying medical illness.

If pregnant or breast-feeding,

ask a health professional before use.

Keep out of reach of children.

In case of overdose, get medical help or contact a Poison Control Center right away.

Directions

- do not take more than directed
- adults and children 12 years and over: take 2 caplets (50 mg) at bedtime if needed, or as directed by a doctor
- children under 12 years: do not use

Other information

- each caplet contains: calcium 65 mg
- avoid excessive heat (greater than 100°F) or humidity
- store at 25°C (77°F); excursions permitted between 15°-30°C (59°-86°F)
- use by expiration date on package

Inactive ingredients

corn starch, D&C red #27 aluminum lake, dibasic calcium phosphate dihydrate, FD&C blue #2 aluminum lake, magnesium stearate, microcrystalline cellulose, polyethylene glycol, polyvinyl alcohol, silicon dioxide, talc, titanium dioxide

Questions or comments?

1-888-423-0139

Principal display panel

TopCare®
health

NDC 36800-672-06

COMPARE TO
VICKS® ZzzQUIL®
ACTIVE INGREDIENT*

NIGHTTIME
Sleep Aid

DIPHENHYDRAMINE HCl, 25 mg

NIGHTTIME SLEEP AID

• Non-Habit Forming
• Not for Treating Pain,
Cold or Flu

200 CAPLETS

TAMPER EVIDENT: DO NOT USE IF IMPRINTED
SAFETY SEAL UNDER CAP IS BROKEN OR MISSING

DISTRIBUTED BY TOPCO ASSOCIATES LLC, ELK GROVE VILLAGE, IL 60007
©TOPCO LNKA0521 QUESTIONS? 1-888-423-0139
topcare@topco.com www.topcarebrand.com
Visit here for more information:
http://topbrnds.com/48ZZY7

√ QUALITY GUARANTEED

*This product is not manufactured or distributed by The Procter
& Gamble Company, owner of the registered trademark VICKS®
ZzzQuil®.

50844 REV0419B67206

Top Care 44-672